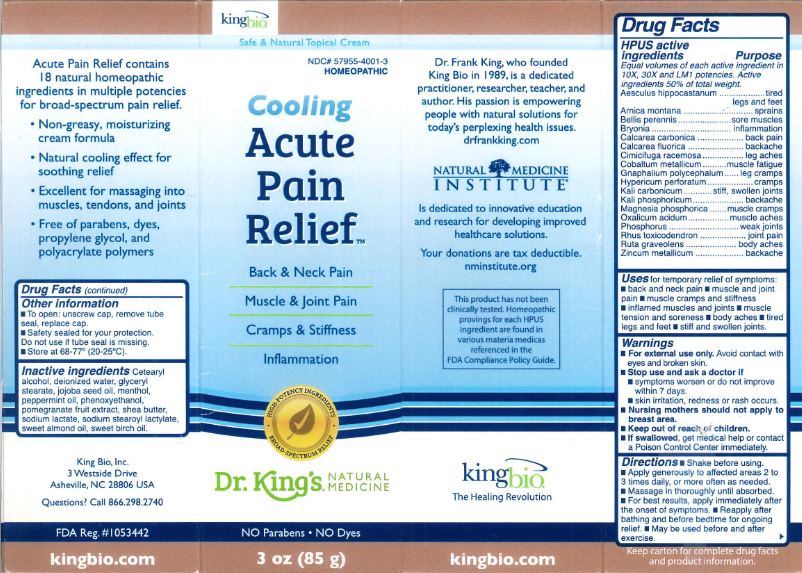 DRUG LABEL: Cooling Acute Pain Relief
NDC: 57955-4001 | Form: CREAM
Manufacturer: King Bio Inc.
Category: homeopathic | Type: HUMAN OTC DRUG LABEL
Date: 20180220

ACTIVE INGREDIENTS: HORSE CHESTNUT 10 [hp_X]/85 g; ARNICA MONTANA 10 [hp_X]/85 g; BELLIS PERENNIS 10 [hp_X]/85 g; BRYONIA ALBA ROOT 10 [hp_X]/85 g; OYSTER SHELL CALCIUM CARBONATE, CRUDE 10 [hp_X]/85 g; CALCIUM FLUORIDE 10 [hp_X]/85 g; BLACK COHOSH 10 [hp_X]/85 g; COBALT 10 [hp_X]/85 g; PSEUDOGNAPHALIUM OBTUSIFOLIUM 10 [hp_X]/85 g; HYPERICUM PERFORATUM 10 [hp_X]/85 g; POTASSIUM CARBONATE 10 [hp_X]/85 g; POTASSIUM PHOSPHATE, DIBASIC 10 [hp_X]/85 g; MAGNESIUM PHOSPHATE, DIBASIC TRIHYDRATE 10 [hp_X]/85 g; OXALIC ACID DIHYDRATE 10 [hp_X]/85 g; PHOSPHORUS 10 [hp_X]/85 g; TOXICODENDRON PUBESCENS LEAF 10 [hp_X]/85 g; RUTA GRAVEOLENS FLOWERING TOP 10 [hp_X]/85 g; ZINC 10 [hp_X]/85 g
INACTIVE INGREDIENTS: CETOSTEARYL ALCOHOL; WATER; GLYCERYL MONOSTEARATE; JOJOBA OIL; MENTHOL; PEPPERMINT OIL; PHENOXYETHANOL; POMEGRANATE; SHEA BUTTER; SODIUM LACTATE; SODIUM STEAROYL LACTYLATE; ALMOND OIL; METHYL SALICYLATE

Cooling Acute Pain Relief

ACTIVE INGREDIENT

Drug Facts__________________________________________________________________________________________________________

HPUS active ingredients:

Equal volumes of each active ingredient in 10X, 30X and LM1 potencies. Active ingredients 50% of total weight.

Aesculus hippocastanum, Arnica montana, Bellis perennis, Bryonia, Calcarea carbonica, Calcarea fluorica, Cimicifuga racemosa, Cobaltum metallicum, Gnaphalium polycephalum, Hypericum perforatum, Kali carbonicum, Kali phosphoricum, Magnesia phosphorica, Oxalicum acidum, Phosphorus, Rhus toxicodendron, Ruta graveolens, Zincum metallicum.

INDICATIONS AND USAGE

Uses: for temporary relief of symptoms: •back and neck pain •muscle and joint pain •muscle cramps and stiffness •inflamed muscles and joints •muscle tension and soreness •body aches •tired legs and feet •stiff and swollen joints

Warnings:

- For external use only. Avoid contact with eyes and broken skin.
- Stop use and ask a doctor if •symptoms worsen or do not improve within 7 days. •skin irritation, redness or rash occurs.
- Nursing mothers should not apply to breast area.
- Keep out of reach of children.
- If swallowed, get medical help or contact a Poison Control Center immediately.

- Keep out of reach of children.

Directions:

•Shake before using. •Apply generously to affected areas 2 to 3 times daily, or more often as needed. •Massage in thoroughly until absorbed. •For best results, apply immediately after the onset of symptoms. •Reapply after bathing and before bedtime for ongoing relief. •May be used before and after exercise.

Other information:

- To open: unscrew cap, remove tube seal, replace cap.
- Safety sealed for your protection.
- Do not use if tube seal is missing.
- Store at 68-77° (20-25°C).

INACTIVE INGREDIENT

Inactive ingredients: Cetearyl alcohol, deionized water, glyceryl stearate, jojoba seed oil, menthol, peppermint oil, phenoxyethanol, pomegranate fruit extract, shea butter, sodium lactate, sodium stearoyl lactylate, sweet almond oil, sweet birch oil.

Drug Facts

__________________________________________________________________________________________________________________

HPUS active ingredients Purpose

Equal volumes of each active ingredient in 10X, 30X and LM1 potencies.

Active ingredients 50% of total weight.

Aesculus hippocastanum..........................................................tired legs and feet

Arnica montana......................................................................sprains

Bellis perennis........................................................................sore muscles

Bryonia..................................................................................inflammation

Calcarea carbonica..................................................................back pain

Calcarea fluorica.....................................................................backache

Cimicifuga racemosa...............................................................leg aches

Cobaltum metallicum..............................................................muscle fatigue

Gnaphalium polycephalum.......................................................leg cramps

Hypericum perforatum............................................................cramps

Kali carbonicum.....................................................................stiff, swollen joints

Kali phosphoricum..................................................................backache

Magnesia phosphorica.............................................................muscle cramps

Oxalicum acidum....................................................................muscle aches

Phosphorus............................................................................weak joints

Rhus toxicodendron................................................................joint pain

Ruta graveolens.....................................................................body aches

Zincum metallicum.................................................................backache